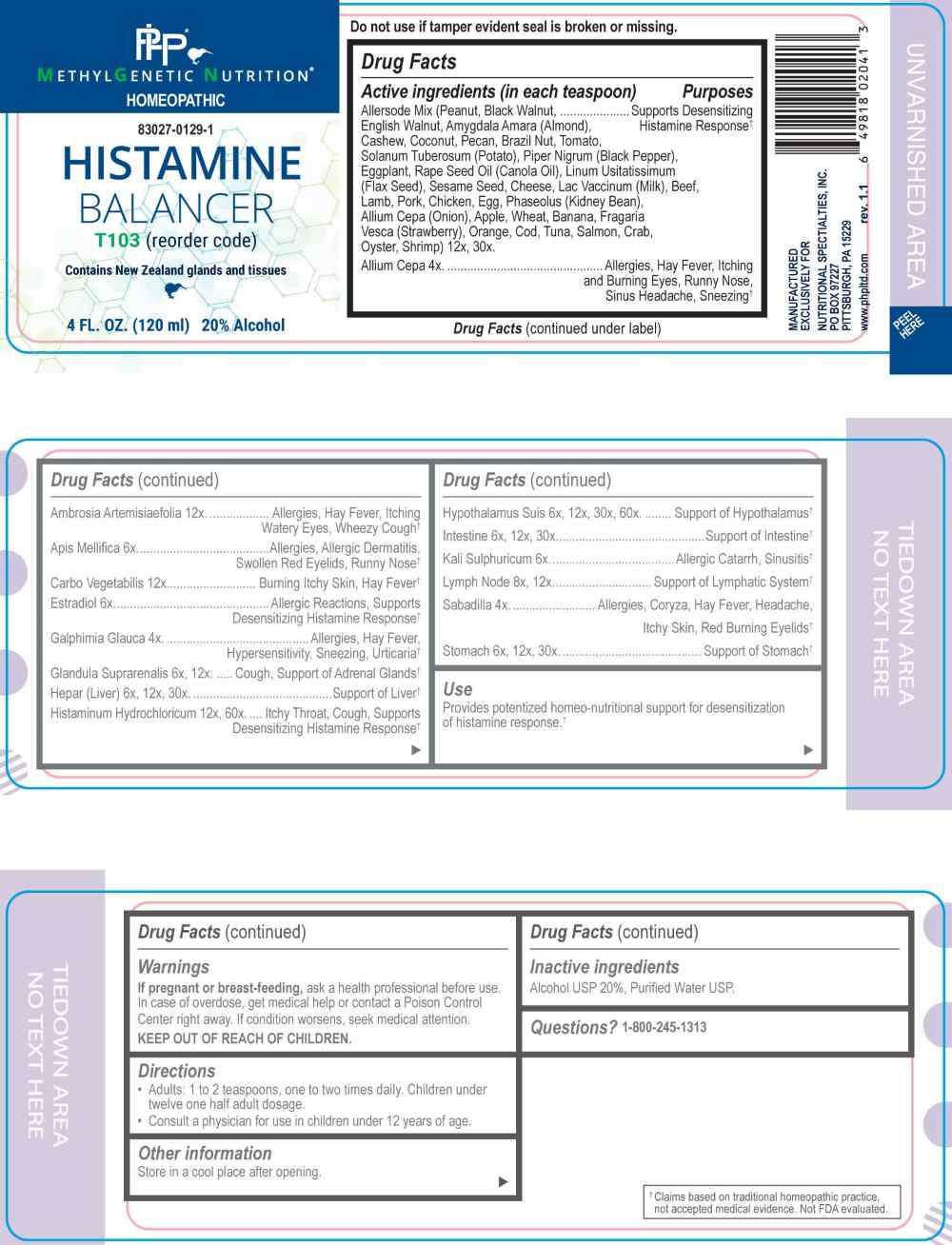 DRUG LABEL: Histamine Balancer
NDC: 83027-0129 | Form: LIQUID
Manufacturer: Nutritional Specialties, Inc.
Category: homeopathic | Type: HUMAN OTC DRUG LABEL
Date: 20251119

ACTIVE INGREDIENTS: ONION 4 [hp_X]/1 mL; GALPHIMIA GLAUCA FLOWERING TOP 4 [hp_X]/1 mL; SCHOENOCAULON OFFICINALE SEED 4 [hp_X]/1 mL; APIS MELLIFERA 6 [hp_X]/1 mL; ESTRADIOL 6 [hp_X]/1 mL; POTASSIUM SULFATE 6 [hp_X]/1 mL; BOS TAURUS ADRENAL GLAND 12 [hp_X]/1 mL; HEPARIN, BOVINE 6 [hp_X]/1 mL; PORK INTESTINE 6 [hp_X]/1 mL; SUS SCROFA STOMACH 6 [hp_X]/1 mL; SUS SCROFA HYPOTHALAMUS 6 [hp_X]/1 mL; SUS SCROFA LYMPH 8 [hp_X]/1 mL; AMBROSIA ARTEMISIIFOLIA WHOLE 12 [hp_X]/1 mL; ACTIVATED CHARCOAL 12 [hp_X]/1 mL; PEANUT 12 [hp_X]/1 mL; BLACK WALNUT 12 [hp_X]/1 mL; ENGLISH WALNUT 12 [hp_X]/1 mL; ALMOND 12 [IR]/1 mL; BITTER ALMOND 12 [hp_X]/1 mL; CASHEW 12 [hp_X]/1 mL; COCONUT 12 [hp_X]/1 mL; PECAN 12 [hp_X]/1 mL; BRAZIL NUT 12 [hp_X]/1 mL; TOMATO 12 [hp_X]/1 mL; SOLANUM TUBEROSUM WHOLE 12 [hp_X]/1 mL; GREEN PEPPERCORN 12 [hp_X]/1 mL; EGGPLANT 12 [hp_X]/1 mL; CANOLA OIL 12 [hp_X]/1 mL; FLAX SEED 12 [hp_X]/1 mL; SESAME SEED 12 [hp_X]/1 mL; CASEIN, LACTOCOCCUS LACTIS CULTURED, PENICILLIUM ROQUEFORTI CULTURED, AGED 12 [hp_X]/1 mL; COW MILK 12 [hp_X]/1 mL; BEEF 12 [hp_X]/1 mL; LAMB 12 [hp_X]/1 mL; PORK 12 [hp_X]/1 mL; CHICKEN 12 [hp_X]/1 mL; EGG 12 [hp_X]/1 mL; KIDNEY BEAN 12 [hp_X]/1 mL; APPLE 12 [hp_X]/1 mL; WHEAT 12 [hp_X]/1 mL; BANANA 12 [hp_X]/1 mL; FRAGARIA VESCA FRUIT 12 [hp_X]/1 mL; ORANGE 12 [hp_X]/1 mL; ATLANTIC COD 12 [hp_X]/1 mL; NORTHERN BLUEFIN TUNA 12 [hp_X]/1 mL; ATLANTIC SALMON 12 [hp_X]/1 mL; EDIBLE ROCK CRAB 12 [hp_X]/1 mL; PACIFIC OYSTER 12 [hp_X]/1 mL; COMMON SHRIMP 12 [hp_X]/1 mL; HISTAMINE DIHYDROCHLORIDE 12 [hp_X]/1 mL
INACTIVE INGREDIENTS: WATER; ALCOHOL

DRUG FACTS:

ACTIVE INGREDIENTS:

Allersode Mix – (Peanut, Black Walnut, English Walnut, Amygdale Amara (Almond), Cashew, Coconut, Pecan, Brazil Nut, Tomato, Solanum Tuberosum (Potato), Piper Nigrum (Black Pepper), Eggplant, Rape Seed Oil (Canola Oil), Linum Usitatissimum (Flax Seed), Sesame Seed, Cheese, Lac Vaccinum (Milk), Beef, Lamb, Pork, Chicken, Egg, Phaseolus (Kidney Bean), Allium Cepa (Onion), Apple, Wheat, Banana, Fragaria Vesca (Strawberry), Orange, Cod, Tuna, Salmon, Crab, Oyster, Shrimp) 12X, 30X, Allium Cepa 4X, Ambrosia Artemisiaefolia 12X, Apis Mellifica 6X, Carbo Vegetabilis 12X, Estradiol 6X, Galphimia Glauca 4X, Glandula Suprarenalis 6X, 12X, Hepar (Liver) 6X, 12X, 30X, Histaminum Hydrochloricum 12X, 60X, Hypothalamus Suis 6X, 12X, 30X, 60X, Intestine 6X, 12X, 30X, Kali Sulphuricum 6X, Lymph Node 8X, 12X, Sabadilla 4X, Stomach 6X, 12X, 30X.

PURPOSE:

Allersode Mix – (Peanut, Black Walnut, English Walnut, Amygdale Amara (Almond), Cashew, Coconut, Pecan, Brazil Nut, Tomato, Solanum Tuberosum (Potato), Piper Nigrum (Black Pepper), Eggplant, Rape Seed Oil (Canola Oil), Linum Usitatissimum (Flax Seed), Sesame Seed, Cheese, Lac Vaccinum (Milk), Beef, Lamb, Pork, Chicken, Egg, Phaseolus (Kidney Bean), Allium Cepa (Onion), Apple, Wheat, Banana, Fragaria Vesca (Strawberry), Orange, Cod, Tuna, Salmon, Crab, Oyster, Shrimp) – Supports Desensitizing Histamine Response,† Allium Cepa – Allergies, Hay Fever, Itching and Burning Eyes, Runny Nose, Sinus Headache, Sneezing,† Ambrosia Artemisiaefolia – Allergies, Hay Fever, Itching Watery Eyes, Wheezy Cough,† Apis Mellifica – Allergies, Allergic Dermatitis, Swollen Red Eyelids, Runny Nose,† Carbo Vegetabilis – Burning Itchy Skin, Hay Fever,† Estradiol – Allergic Reactions, Supports Desensitizing Histamine Response,† Galphimia Glauca – Allergies, Hay Fever, Hypersensitivity, Sneezing, Urticaria,† Glandula Suprarenalis – Cough, Support of Adrenal Glands,† Hepar (Liver) – Support of Liver,† Histaminum Hydrochloricum – Itchy Throat, Cough, Supports Desensitizing Histamine Response,† Hypothalamus Suis – Support of Hypothalamus,† Intestine – Support of Intestine,† Kali Sulphuricum – Allergic Catarrh, Sinusitis,† Lymph Node – Support of Lymphatic System,† Sabadilla – Allergies, Coryza, Hay Fever, Headache, Itchy Skin, Red Burning Eyelids,† Stomach – Support of Stomach†

†Claims based on traditional homeopathic practice, not accepted medical evidence. Not FDA evaluated.

USE:

Provides potentized homeo-nutritional support for desensitization of histamine response.†

†Claims based on traditional homeopathic practice, not accepted medical evidence. Not FDA evaluated.

WARNINGS:

If pregnant or breast-feeding, ask a health professional before use.

In case of overdose, get medical help or contact a Poison Control Center right away.

If condition worsens, seek medical attention.

KEEP OUT OF REACH OF CHILDREN

Do not use if tamper evident seal is broken or missing.

Store in a cool place after opening

KEEP OUT OF REACH OF CHILDREN:

In case of overdose, get medical help or contact a Poison Control Center right away.

DIRECTIONS:

• Adults: 1 to 2 teaspoons, one to two times daily. Children under twelve one half adult dosage.

Consult a physician for use in children under 12 years of age.

INACTIVE INGREDIENTS:

Alcohol USP 20%, Purified Water USP.

QUESTIONS:

MANUFACTURED EXCLUSIVELY FOR

NUTRITIONAL SPECIALTIES, INC.

PO BOX 97227

PITTSBURG, PA 15229

www.phpltd.com

1-800-245-1313

PACKAGE LABEL DISPLAY:

METHYL GENETIC NUTRITION

HOMEOPATHIC

83027-0129-1

HISTAMINE

BALANCER

4 FL. OZ (120 ml)